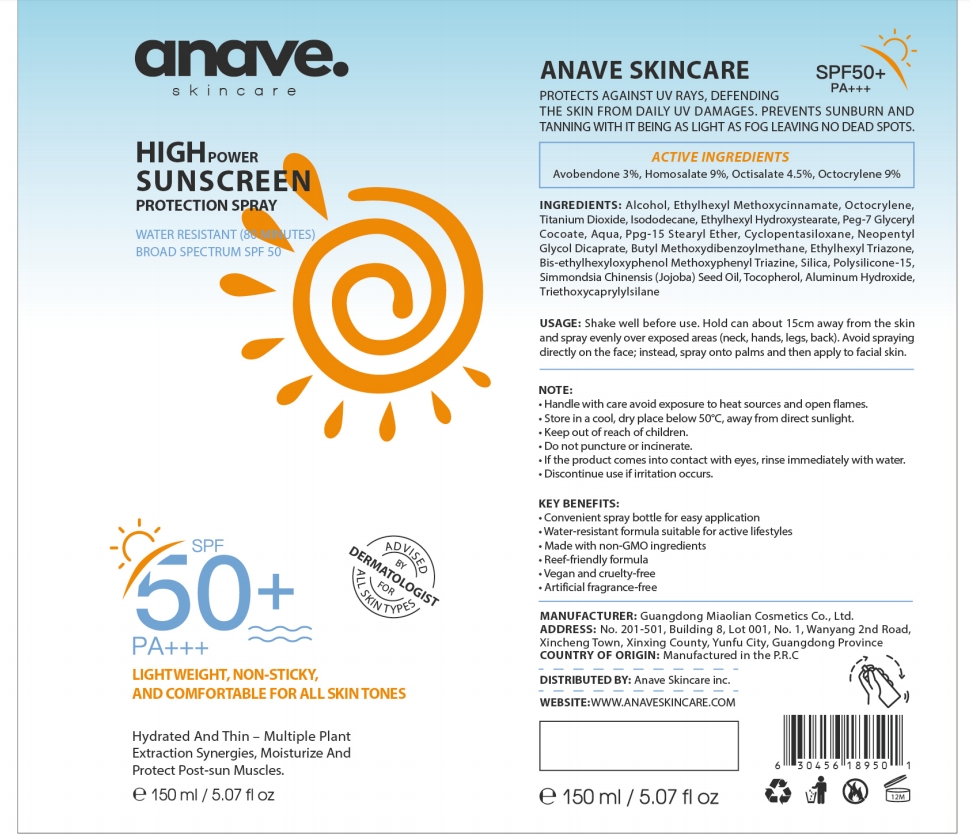 DRUG LABEL: Anave Skincare Sunscreen
NDC: 84507-002 | Form: AEROSOL
Manufacturer: Guangdong Miaolian Cosmetics Co., Ltd.
Category: otc | Type: HUMAN OTC DRUG LABEL
Date: 20240726

ACTIVE INGREDIENTS: HOMOSALATE 9 g/100 mL; AVOBENZONE 3 g/100 mL; OCTISALATE 4.5 g/100 mL; OCTOCRYLENE 9 g/100 mL
INACTIVE INGREDIENTS: SILICON DIOXIDE; TITANIUM DIOXIDE; JOJOBA OIL; ALCOHOL; OCTINOXATE; CYCLOMETHICONE 5; BEMOTRIZINOL; PEG-7 GLYCERYL COCOATE; ETHYLHEXYL TRIAZONE; NEOPENTYL GLYCOL DICAPRATE; ISODODECANE; ETHYLHEXYL HYDROXYSTEARATE; PPG-15 STEARYL ETHER; WATER; POLYSILICONE-15

USAGE

Shake well before use. Hold can about 15cm away from the skinand spray evenly over exposed areas (neck, hands, legs, back). Avoid sprayingdirectly on the face; instead, spray onto palms and then apply to facial skin.

NOTE

.Handle with care avoid exposure to heat sources and open fames..Store in a cool, dry place below 50°C, away from direct sunlight..Keep outofreach of children.
.Do not puncture orincinerate.
. lf the product comes into contact with eyes, rinse immediately with water.
.Discontinue use ifirritation occurs.

INGREDIENTS

Alcohol, Ethylhexyl Methoxycinnamate, Octocrylene,Titanium Dioxide, lsododecane, Ethylhexyl Hydroxystearate, Peg-7 GlycerylCocoate,Aqua, Ppg-15 Stearyl Ether, Cyclopentasiloxane, NeopentylGlycol Dicaprate, Butyl Methoxydibenzoylmethane, Ethylhexyl Triazone,Bis-ethylhexyloxyphenol Methoxyphenyl Triazine, Silica, Polysilicone-15.Simmondsia Chinensis (Jojoba) Seed Oil, Tocopherol, Aluminum Hydroxide,Triethoxycaprylylsilane

INDICATIONS AND USAGE

Hold can about 15cm away from the skinand spray evenly over exposed areas (neck, hands, legs, back). Avoid sprayingdirectly on the face; instead, spray onto palms and then apply to facial skin.

.Keep out ofreach of children.

PURPOSE

Protects against uv rays, defendingthe skin from daily uv damages. prevents sunburn andtanning with it being as light as fog leaving no dead spots.

ACTIVEINGREDIENTS

Avobendone 3%,Homosalate 9%, Octisalate 4.5%, Octocrylene 9%

package

WHEN USING SECTION

Active Ingredients：Avobendone 3%, Homosalate 9%, Octisalate 4.5%, Octocrylene 9%

INGREDIENTS: Alcohol, Ethylhexyl Methoxycinnamate, Octocrylene, Titanium Dioxide, Isododecane, Ethylhexyl Hydroxystearate, Peg-7 Glyceryl Cocoate, Aqua, Ppg-15 Stearyl Ether, Cyclopentasiloxane, Neopentyl Glycol Dicaprate, Butyl Methoxydibenzoylmethane, Ethylhexyl Triazone,Bis-ethylhexyloxyphenol Methoxyphenyl Triazine, Silica, Polysilicone-15,Simmondsia Chinensis (Jojoba) Seed Oil

USAGE: Shake well before use. Hold can about 15cm away from the skin and spray evenly over exposed areas (neck, hands, legs, back). Avoid spraying directly on the face; instead, spray onto palms and then apply to facial skin.

NOTE:
• Handle with care avoid exposure to heat sources and open flames.
• Store in a cool, dry place below 50°C, away from direct sunlight.
• Keep out of reach of children.
• Do not puncture or incinerate.
• If the product comes into contact with eyes, rinse immediately with water.
• Discontinue use if irritation occurs.

KEY BENEFITS:
• Convenient spray bottle for easy application
• Water-resistant formula suitable for active lifestyles
• Made with non-GMO ingredients
• Reef-friendly formula
• Vegan and cruelty-free
• Artificial fragrance-free

MANUFACTURER: Guangdong Miaolian Cosmetics Co., Ltd.
ADDRESS: No. 201-501, Building 8, Lot 001, No. 1, Wanyang 2nd Road,
Xincheng Town, Xinxing County, Yunfu City, Guangdong Province
COUNTRY OF ORIGIN: Manufactured in the P.R.C

DISTRIBUTED BY: Anave Skincare inc.
WEBSITE:WWW.ANAVESKINCARE.COM